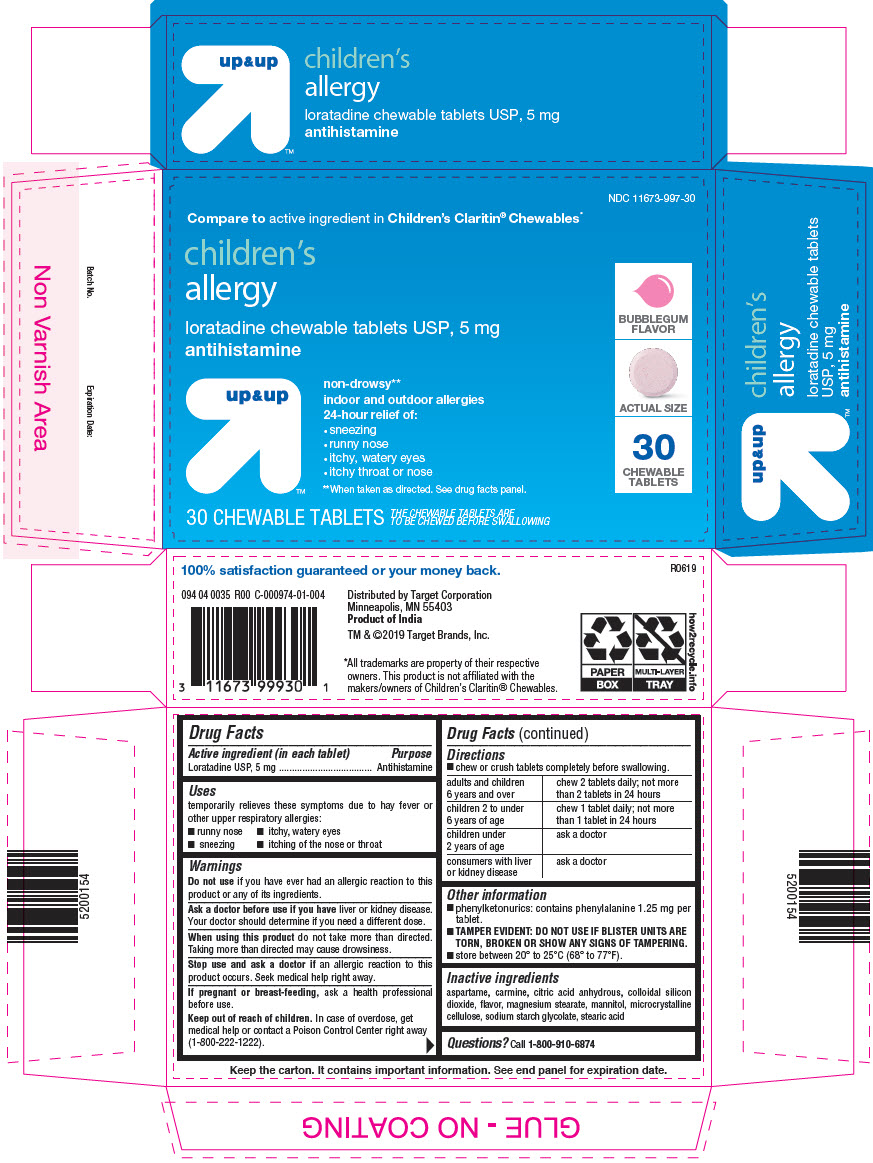 DRUG LABEL: CHILDRENS LORATADINE
NDC: 11673-997 | Form: TABLET, CHEWABLE
Manufacturer: TARGET CORPORATION
Category: otc | Type: HUMAN OTC DRUG LABEL
Date: 20241227

ACTIVE INGREDIENTS: LORATADINE 5 mg/1 1
INACTIVE INGREDIENTS: ASPARTAME; COCHINEAL; ANHYDROUS CITRIC ACID; SILICON DIOXIDE; MAGNESIUM STEARATE; MANNITOL; MICROCRYSTALLINE CELLULOSE; SODIUM STARCH GLYCOLATE TYPE A POTATO; STEARIC ACID

CHILDREN'S LORATADINE

Drug Facts

Active ingredient (in each tablet)

Loratadine USP, 5 mg

Purpose

Antihistamine

Uses

temporarily relieves these symptoms due to hay fever or other upper respiratory allergies:

- runny nose
- itchy, watery eyes
- sneezing
- itching of the nose or throat

Warnings

DO NOT USE

Do not useif you have ever had an allergic reaction to this product or any of its ingredients.

Ask a doctor before use if you haveliver or kidney disease. Your doctor should determine if you need a different dose.

WHEN USING

When using this productdo not take more than directed. Taking more than directed may cause drowsiness.

Stop use and ask a doctor ifan allergic reaction to this product occurs. Seek medical help right away.

PREGNANCY OR BREAST FEEDING

If pregnant or breast-feeding,ask a health professional before use.

Keep out of reach of children.In case of overdose, get medical help or contact a Poison Control Center right away (1-800-222-1222).

Directions

- chew or crush tablets completely before swallowing.

adults and children 6 years and over | chew 2 tablets daily; not more than 2 tablets in 24 hours
children 2 to under 6 years of age | chew 1 tablet daily; not more than 1 tablet in 24 hours
children under 2 years of age | ask a doctor
consumers with liver or kidney disease | ask a doctor

Other information

- phenylketonurics: contains phenylalanine 1.25 mg per tablet.
- TAMPER EVIDENT: DO NOT USE IF BLISTER UNITS ARE TORN, BROKEN OR SHOW ANY SIGNS OF TAMPERING.
- store between 20° to 25°C (68° to 77°F).

Inactive ingredients

aspartame, carmine, citric acid anhydrous, colloidal silicon dioxide, flavor, magnesium stearate, mannitol, microcrystalline cellulose, sodium starch glycolate, stearic acid

Questions?

Call 1-800-910-6874

Distributed by Target Corporation
Minneapolis, MN 55403

PRINCIPAL DISPLAY PANEL - 5 mg Tablet Blister Pack Carton

NDC 11673-997-30

Compare to active ingredient in Children's Claritin®Chewables*

children's
allergy

loratadine chewable tablets USP, 5 mg
antihistamine

up&up

non-drowsy**
indoor and outdoor allergies
24-hour relief of:

- sneezing
- runny nose
- itchy, watery eyes
- itchy throat or nose

**When taken as directed. See drug facts panel.

30 CHEWABLE TABLETS

THE CHEWABLE TABLETS ARE
TO BE CHEWED BEFORE SWALLOWING

BUBBLEGUM
FLAVOR

ACTUAL SIZE

30
CHEWABLE
TABLETS